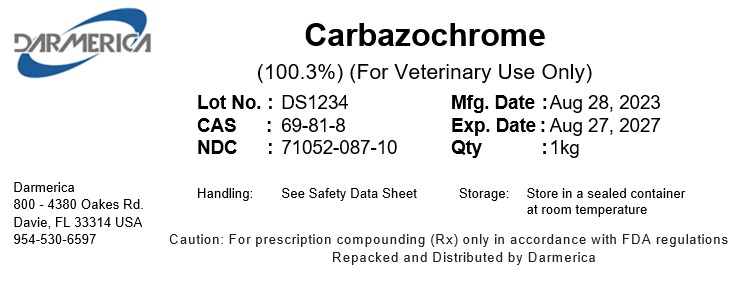 DRUG LABEL: Carbazochrome
NDC: 71052-087 | Form: POWDER
Manufacturer: DARMERICA, LLC
Category: other | Type: BULK INGREDIENT - ANIMAL DRUG
Date: 20241219

ACTIVE INGREDIENTS: CARBAZOCHROME 1000 g/1000 g

Carbazochrome